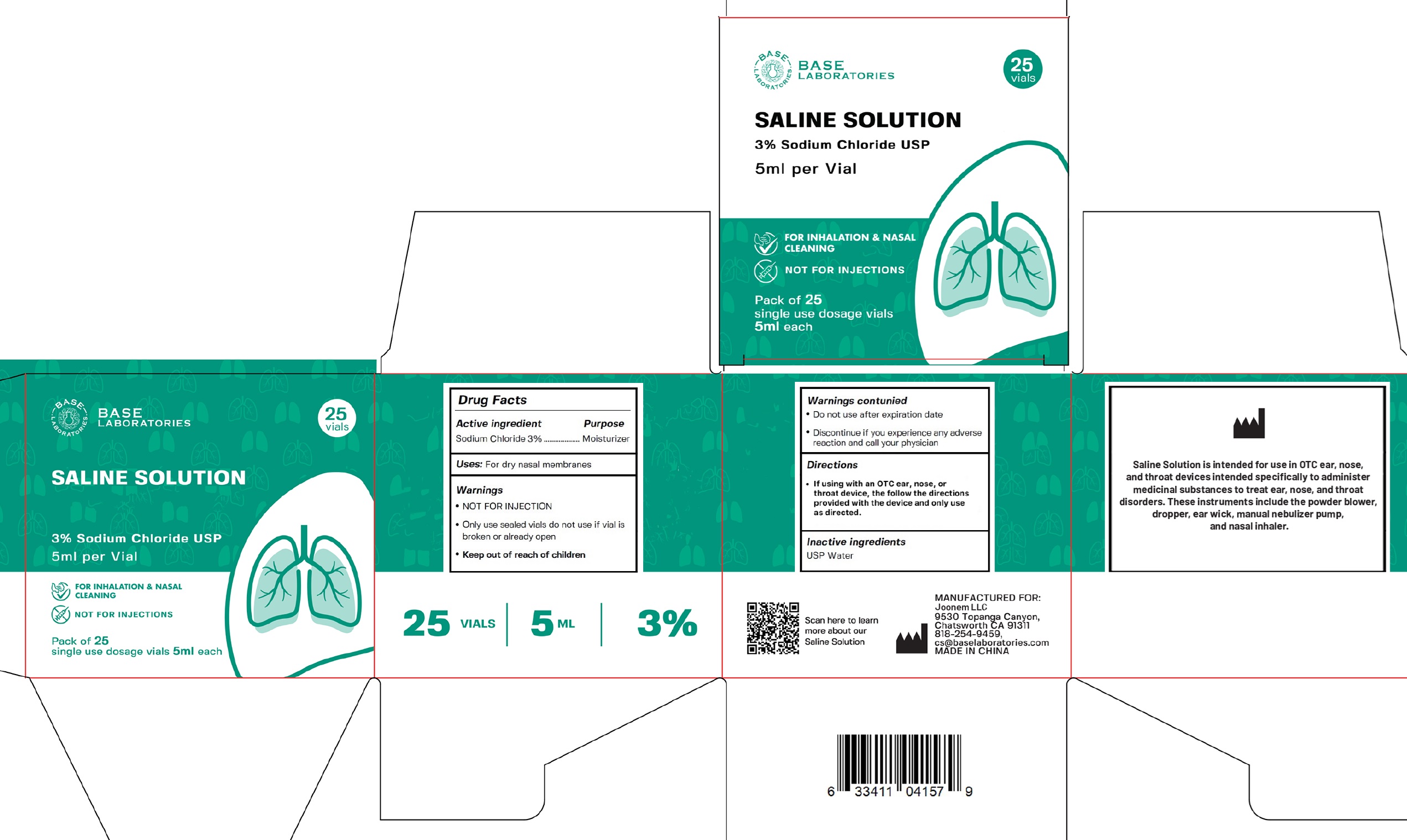 DRUG LABEL: Base Laboratories Saline
NDC: 80327-013 | Form: LIQUID
Manufacturer: Joonem LLC
Category: otc | Type: HUMAN OTC DRUG LABEL
Date: 20241223

ACTIVE INGREDIENTS: SODIUM CHLORIDE 30 mg/1 mL
INACTIVE INGREDIENTS: WATER

Base Laboratories Saline Solution 3% Sodium Chloride

Active ingredient

Sodium Chloride 3%

Purpose

Moisturizer

Uses:

For dry nasal membranes

Warnings

- NOT FOR INJECTION
- Only use sealed vials do not use if vial is broken or already open

• Do not use

after expiration date

- Discontinue if you experience any adverse reaction and call your physician

Directions

- If using with an OTC ear, nose, or throat device, the follow the directions provided with the device and only use as directed.

Inactive ingredients

USP Water